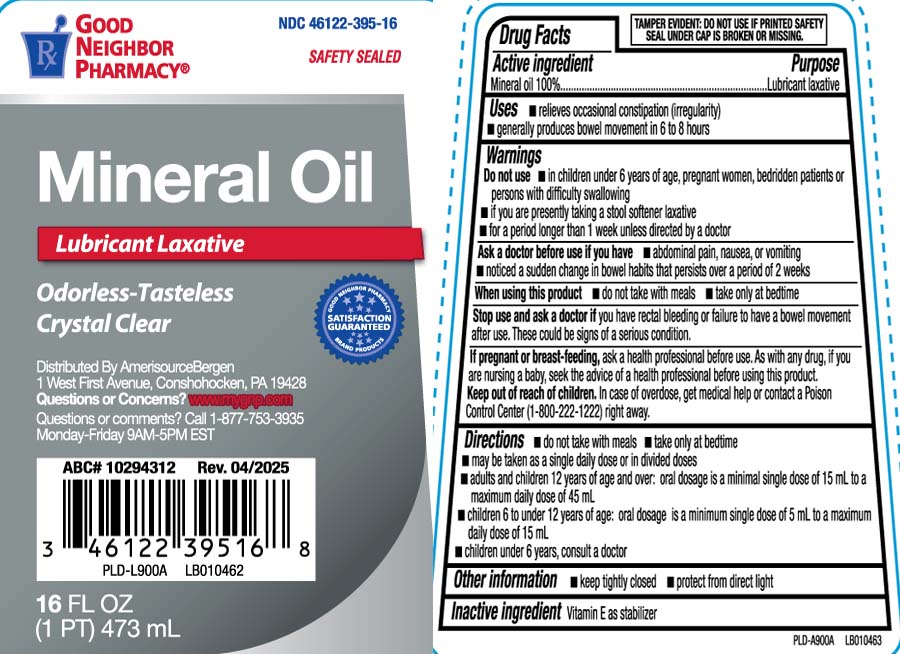 DRUG LABEL: Mineral Oil
NDC: 46122-395 | Form: OIL
Manufacturer: AmerisourceBergen (Good Neighbor Pharmacy) 46122
Category: otc | Type: HUMAN OTC DRUG LABEL
Date: 20250417

ACTIVE INGREDIENTS: MINERAL OIL 100 mg/100 mL
INACTIVE INGREDIENTS: TOCOPHEROL

Drug Facts

Active Ingredient

Mineral Oil, USP 100%

Purpose

Lubricant laxative

Uses

- relieves occasional constipation (irregularity)
- generally produces bowel movement in 6 to 8 hours

Warnings

Do not use

- in children under 12 years of age, pregnant wormen, bedridden patients or aged, or if you have difficulty swallowing
- if you are presently taking a stool softener laxative
- for longer than 1 week

Ask a doctor before use if you have

- abdominal pain, nausea or vomiting
- noticed a sudden change in bowel habits that persists over a period of 2 weeks

When using this product

- do not take with meals
- take only at bedtime

Stop use and ask a doctor if you have

rectal bleeding or failure to have a bowel movement after use. These could be signs of a serious condition.

If pregnant or breast feeding,

ask a health professional before use

Keep out of reach of children

In case of overdose, get medical help or contact a Poison Control center (1-800-222-1222) right away.

Directions

- do not take with meals
- take only at bedtime
- may be taken as a single daily dose or in divided doses
- adults and children 12 years of age and over: oral dosage is a minimum single dose of 15 mL to a maximum daily dose of 45 mL
- children 6 to under 12 years of age: oral dosage is a minimum single dose of 5 mL to a maximum daily dose of 15 mL
- children under 6 years of age: consult a doctor

Other Information

- keep tightly closed
- protect from direct light

Inactive Ingredient

Vitamin E as stabilizer

Principal Display Panel

SAFETY SEALED

Mineral Oil

Lubricant Laxative

Odorless-Tasteless

Crystal Clear

FL OZ (mL)

TAMPER EVIDENT: DO NOT USE IF PRINTED SAFETY SEAL UNDER CAP IS BROKEN OR MISSING

Distributed by AmerisourceBergen

1 West First Avenue, Conshohocken, PA 19428

www.mygnp.com

Questions or comments? Call 1-877-753-3935

Monday-Friday 9AM-5PM EST

Package Label

GOOD NEIGHBOR PHARMACY Mineral Oil